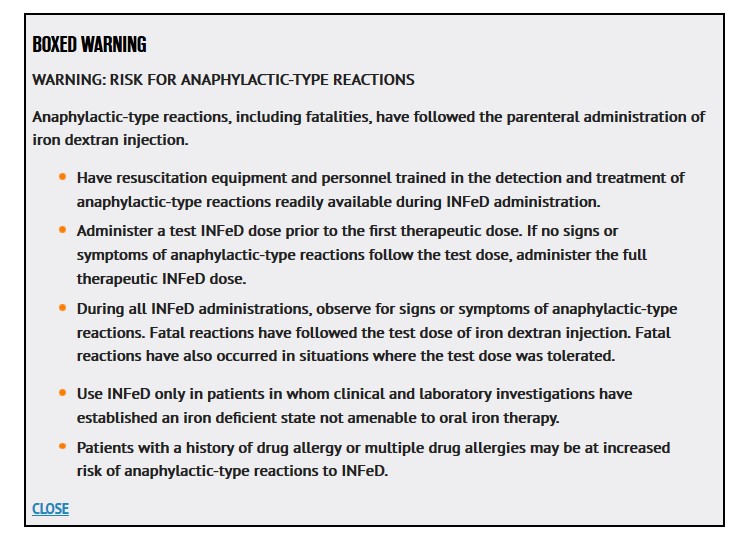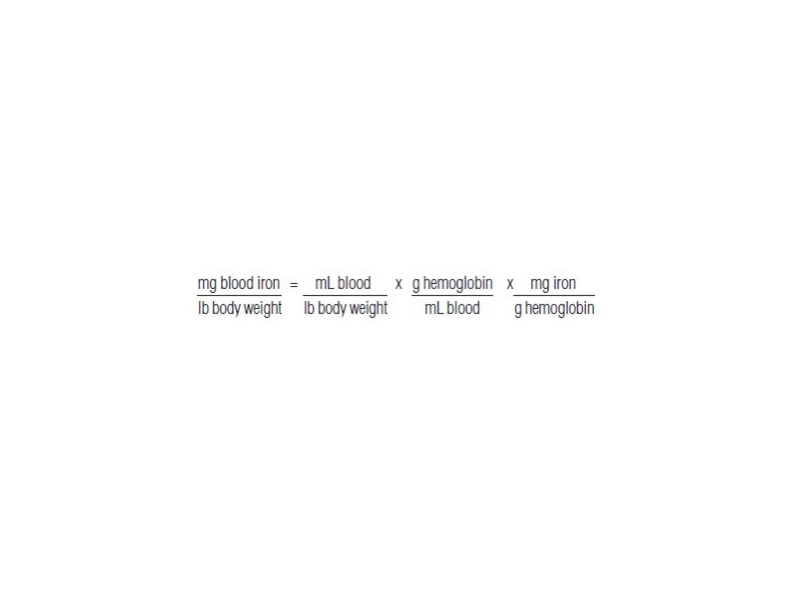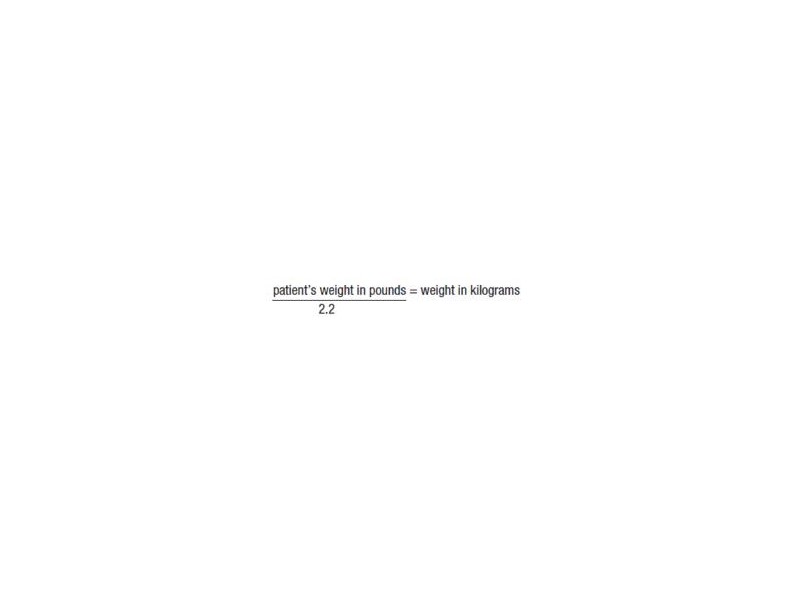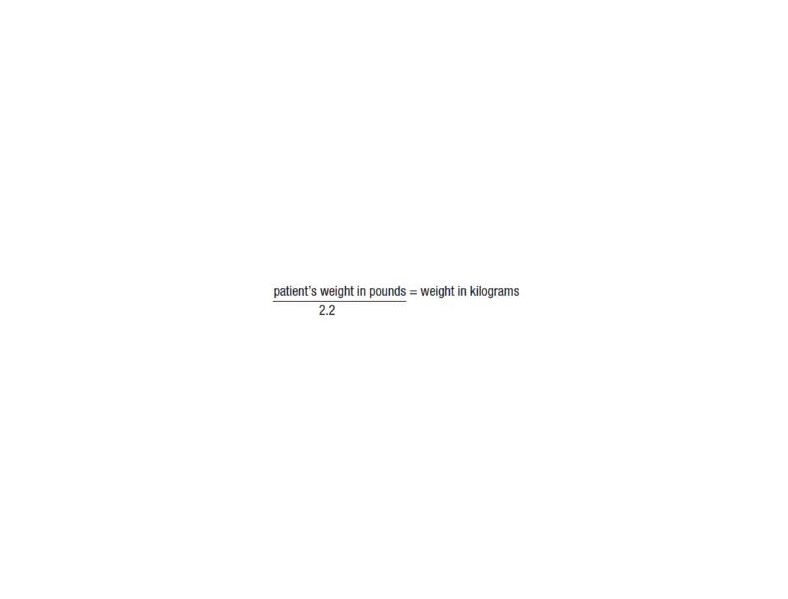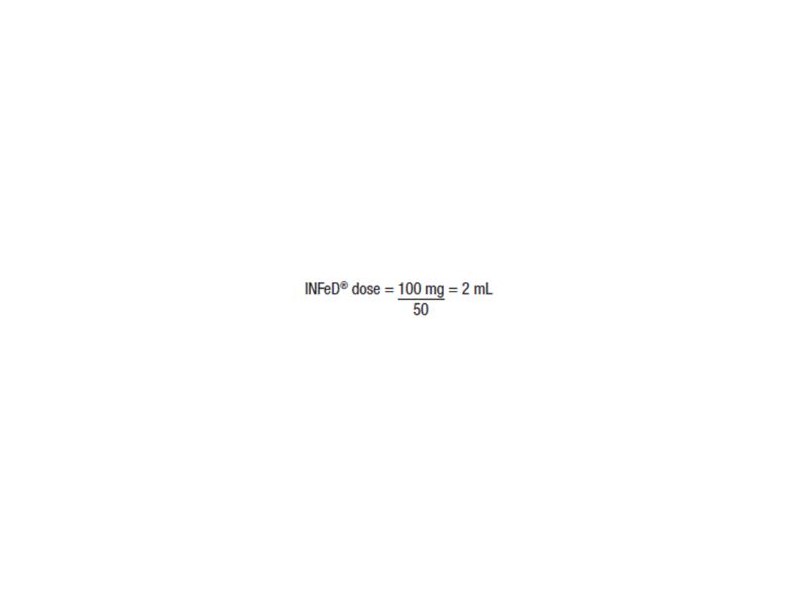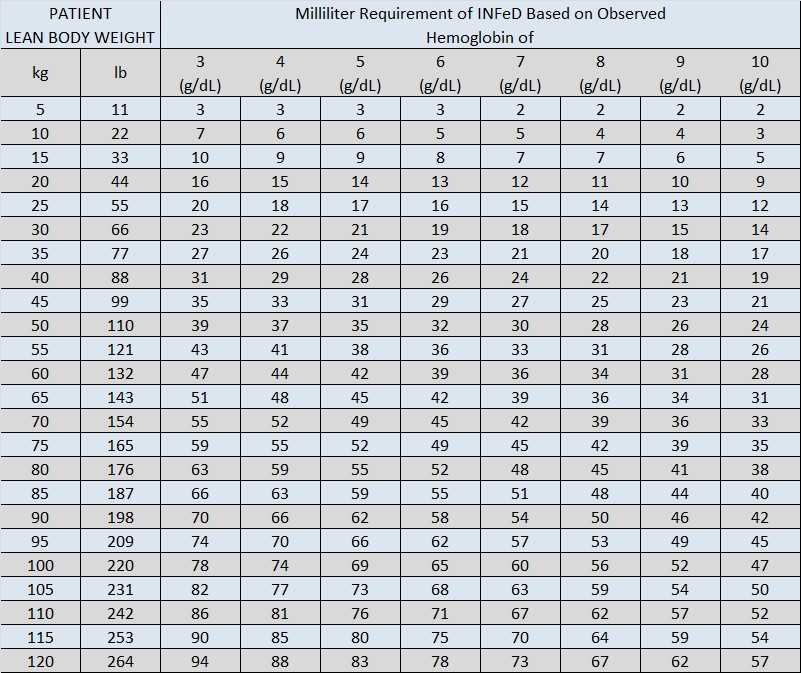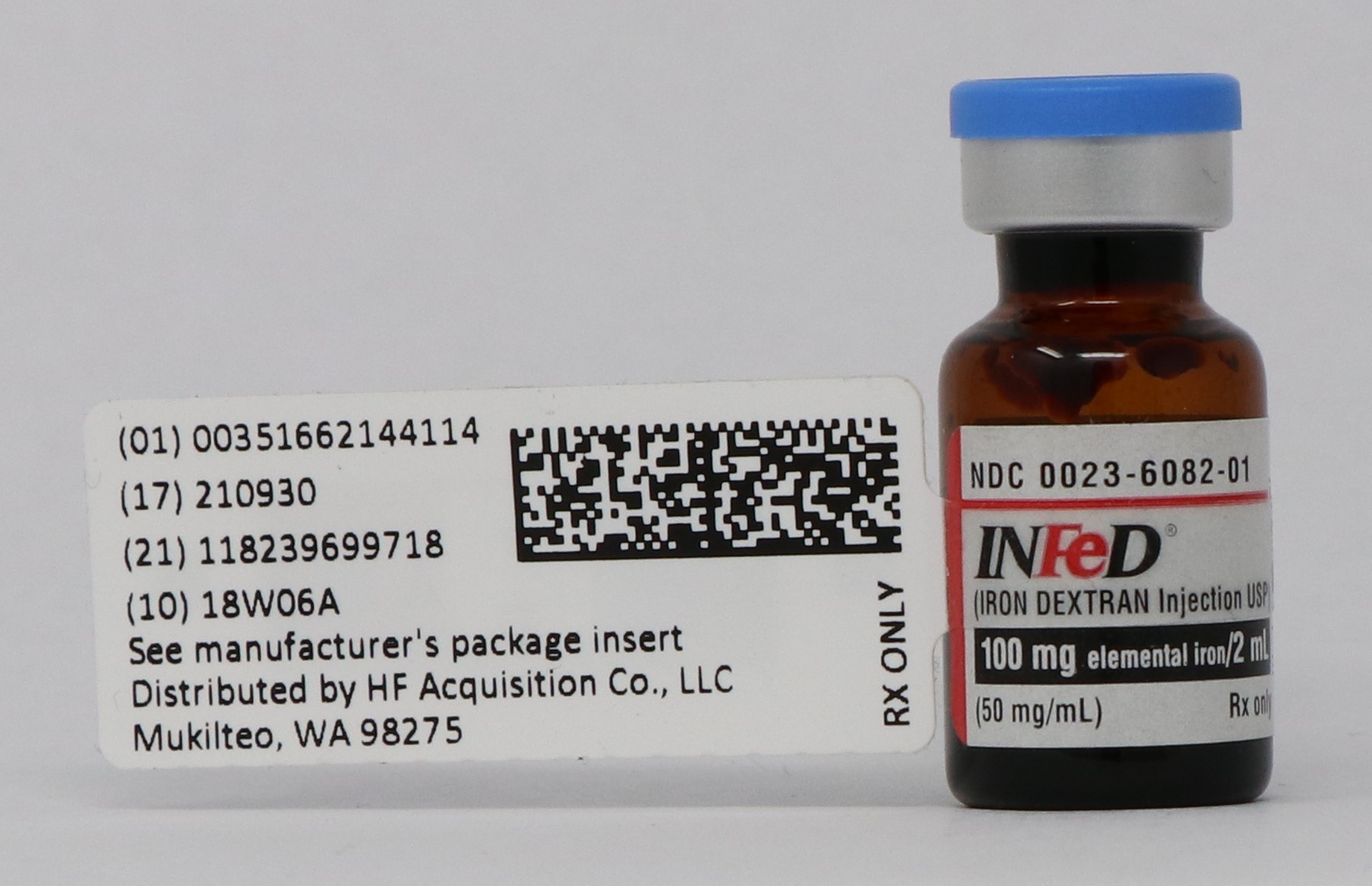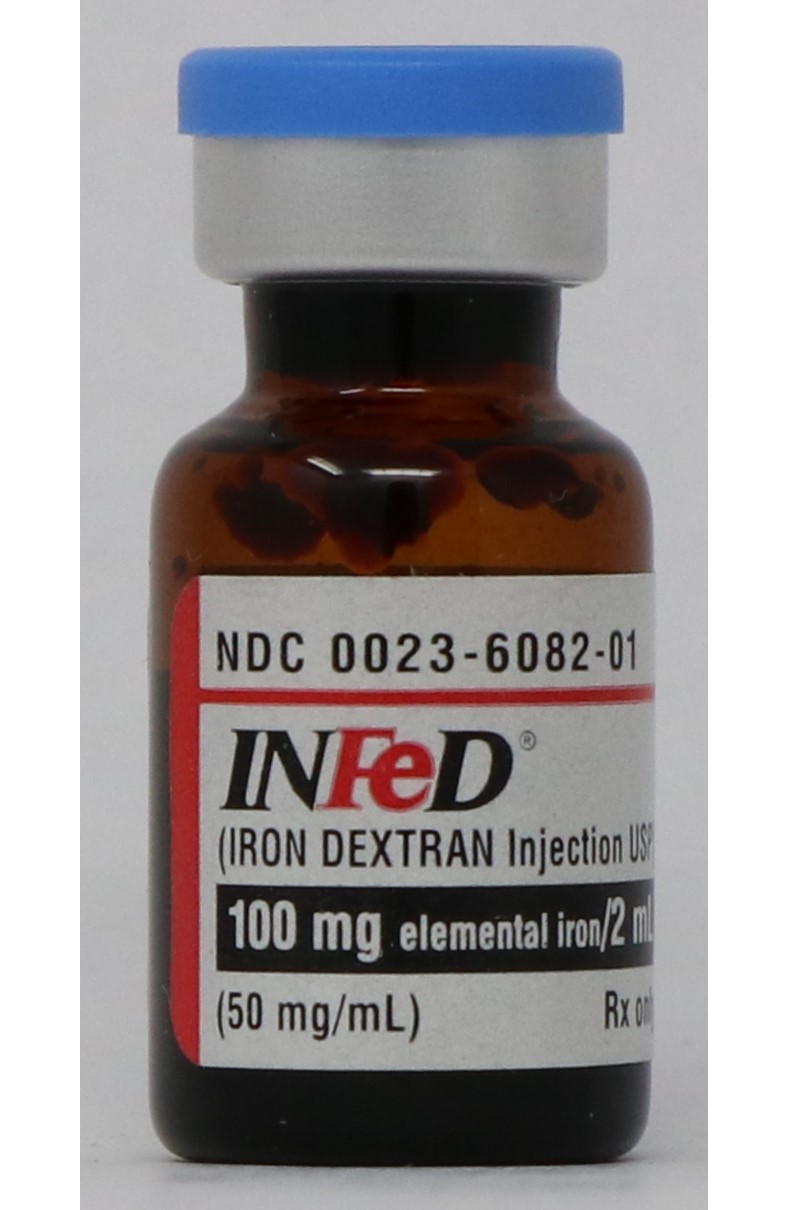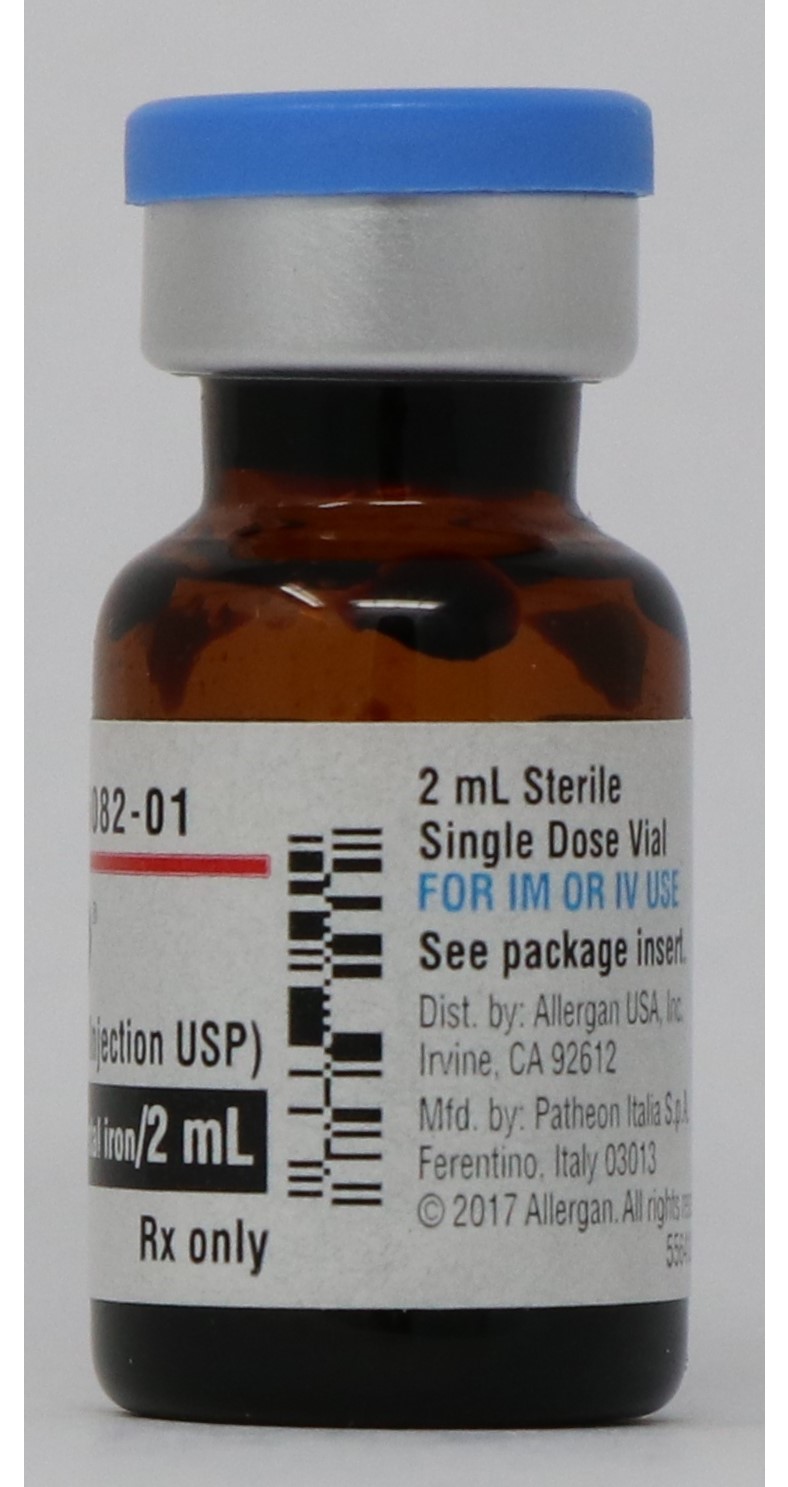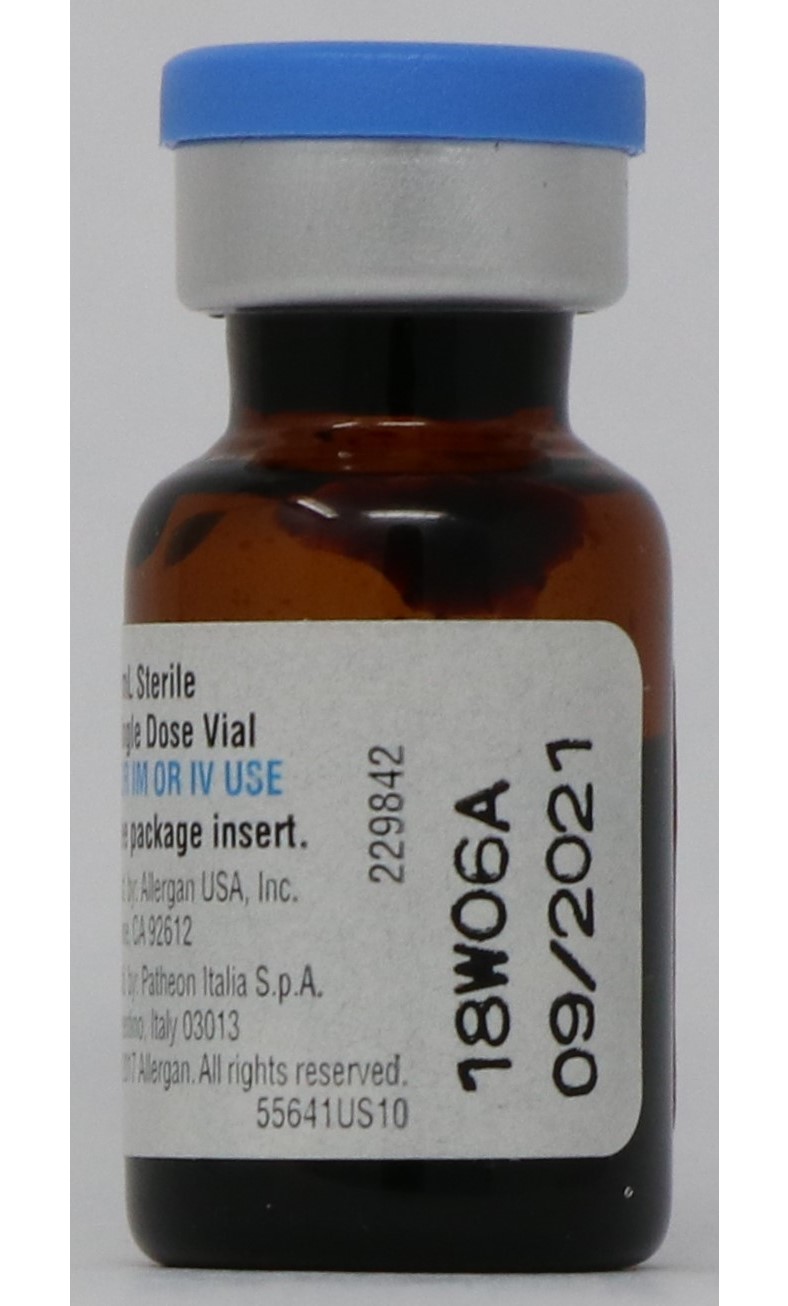 DRUG LABEL: IRON DEXTRAN
NDC: 51662-1441 | Form: INJECTION
Manufacturer: HF Acquisition Co LLC, DBA HealthFirst
Category: prescription | Type: HUMAN PRESCRIPTION DRUG LABEL
Date: 20250108

ACTIVE INGREDIENTS: IRON DEXTRAN 50 mg/1 mL
INACTIVE INGREDIENTS: SODIUM HYDROXIDE

INFED(R) (IRON DEXTRAN INJECTION, USP) 100mg elemental iron/2mL (50mg/mL) 2mL VIAL

DESCRIPTION

INFeD (Iron Dextran Injection USP) is a dark brown, slightly viscous sterile liquid complex of ferric hydroxide and dextran for intravenous or intramuscular use.

Each mL contains the equivalent of 50 mg of elemental iron (as an iron dextran complex), approximately 0.9% sodium chloride, in water for injection. Sodium hydroxide and/or hydrochloric acid may have been used to adjust pH. The pH of the solution is between 4.5 to 7.0.

Therapeutic Class: Hematinic

CLINICAL PHARMACOLOGY

General: After intramuscular injection, iron dextran is absorbed from the injection site into the capillaries and the lymphatic system. Circulating iron dextran is removed from the plasma by cells of the reticuloendothelial system, which split the complex into its components of iron and dextran. The iron is immediately bound to the available protein moieties to form hemosiderin or ferritin, the physiological forms of iron, or to a lesser extent to transferrin. This iron which is subject to physiological control replenishes hemoglobin and depleted iron stores.

Dextran, a polyglucose, is either metabolized or excreted. Negligible amounts of iron are lost via the urinary or alimentary pathways after administration of iron dextran.

The major portion of intramuscular injections of iron dextran is absorbed within 72 hours; most of the remaining iron is absorbed over the ensuing 3 to 4 weeks.

Various studies involving intravenously administered 59Fe iron dextran to iron deficient subjects, some of whom had coexisting diseases, have yielded half-life values ranging from 5 hours to more than 20 hours. The 5-hour value was determined for 59Fe iron dextran from a study that used laboratory methods to separate the circulating 59Fe iron dextran from the transferrin-bound 59Fe. The 20-hour value reflects a half-life determined by measuring total 59Fe, both circulating and bound. It should be understood that these half-life values do not represent clearance of iron from the body. Iron is not easily eliminated from the body and accumulation of iron can be toxic.

In vitro studies have shown that removal of iron dextran by dialysis is negligible.1,2 Six different dialyzer membranes were investigated (polysulfone, cuprophane, cellulose acetate, cellulose triacetate, polymethylmethacrylate and polyacrylonitrile), including those considered high efficiency and high flux.

INDICATIONS & USAGE

Intravenous or intramuscular injections of INFeD are indicated for treatment of patients with documented iron deficiency in whom oral administration is unsatisfactory or impossible.

CONTRAINDICATIONS

Hypersensitivity to the product. All anemias not associated with iron deficiency.

WARNINGS

Risk for Anaphylactic-type Reactions:

Anaphylactic-type reactions, including fatalities have followed the parenteral administration of iron dextran. Always have resuscitation equipment and personnel trained in the detection and treatment of anaphylactic-type reactions readily available during INFeD administration. Prior to the first therapeutic dose, administer a test INFeD dose of 0.5 mL. (See DOSAGE AND ADMINISTRATION.) Although reactions are usually evident within a few minutes, observe patients for at least one hour before administering the therapeutic dose. During all INFeD administrations, observe patients for signs or symptoms of anaphylactic-type reactions. Fatal reactions have followed the test dose of iron dextran and have also occurred in situations where the test dose was tolerated. Use INFeD only in patients in whom clinical and laboratory investigations have established an iron deficient state not amenable to oral iron therapy.

The factors that affect the risk for anaphylactic-type reactions to iron dextran products are not fully known but limited clinical data suggest the risk may be increased among patients with a history of drug allergy or multiple drug allergies. Additionally, concomitant use of angiotensin-converting enzyme inhibitor drugs may increase the risk for reactions to an iron dextran product. The extent of risk for anaphylactic-type reactions following exposure to any specific iron dextran product is unknown and may vary among the products.

Iron dextran products differ in chemical characteristics and may differ in clinical effects. Iron dextran products are not clinically interchangeable.

Delayed Reactions:

Large intravenous doses, such as used with total dose infusions (TDI), have been associated with an increased incidence of adverse effects. The adverse effects frequently are delayed (1-2 days) reactions typified by one or more of the following symptoms: arthralgia, backache, chills, dizziness, moderate to high fever, headache, malaise, myalgia, nausea, and vomiting. The onset is usually 24-48 hours after administration and symptoms generally subside within 3-4 days. The etiology of these reactions is not known. The potential for a delayed reaction must be considered when estimating the risk/benefit of treatment.

The maximum daily dose should not exceed 2 mL undiluted iron dextran.

Risk in Patients with Underlying Conditions:

INFeD should be used with extreme care in patients with serious impairment of liver function. It should not be used during the acute phase of infectious kidney disease.

Adverse reactions experienced following administration of INFeD may exacerbate cardiovascular complications in patients with pre-existing cardiovascular disease.

Carcinogenesis:

A risk of carcinogenesis may attend the intramuscular injection of iron-carbohydrate complexes. Such complexes have been found under experimental conditions to produce sarcoma when large doses or small doses injected repeatedly at the same site were given to rats, mice, and rabbits, and possibly in hamsters.

The long latent period between the injection of a potential carcinogen and the appearance of a tumor makes it impossible to measure accurately the risk in man. There have, however, been several reports in the literature describing tumors at the injection site in humans who had previously received intramuscular injections of iron-carbohydrate complexes.

PRECAUTIONS

General:

Unwarranted therapy with parenteral iron will cause excess storage of iron with the consequent possibility of exogenous hemosiderosis. Such iron overload is particularly apt to occur in patients with hemoglobinopathies and other refractory anemias that might be erroneously diagnosed as iron deficiency anemias.

INFeD should be used with caution in individuals with histories of significant allergies and/or asthma. Anaphylaxis and other hypersensitivity reactions have been reported after uneventful test doses as well as therapeutic doses of iron dextran injection. Therefore, administer a test dose prior to the first therapeutic dose of INFeD. (See BOXED WARNING and DOSAGE AND ADMINISTRATION: Administration.)

Epinephrine should be immediately available in the event of acute hypersensitivity reactions. (Usual adult dose: 0.5 mL of a 1:1000 solution, by subcutaneous or intramuscular injection.) Note: Patients using beta-blocking agents may not respond adequately to epinephrine. Isoproterenol or similar beta-agonist agents may be required in these patients.

Patients with rheumatoid arthritis may have an acute exacerbation of joint pain and swelling following the administration of INFeD.

Reports in the literature from countries outside the United States (in particular, New Zealand) have suggested that the use of intramuscular iron dextran in neonates has been associated with an increased incidence of gram-negative sepsis, primarily due to E. Coli.

Information For Patients:

Patients should be advised of the potential adverse reactions associated with the use of INFeD.

Drug/Laboratory Test Interactions:

Large doses of iron dextran (5 mL or more) have been reported to give a brown color to serum from a blood sample drawn 4 hours after administration.

The drug may cause falsely elevated values of serum bilirubin and falsely decreased values of serum calcium. Serum iron determinations (especially by colorimetric assays) may not be meaningful for 3 weeks following the administration of iron dextran.

Serum ferritin peaks approximately 7 to 9 days after an intravenous dose of INFeD and slowly returns to baseline after about 3 weeks.

Examination of the bone marrow for iron stores may not be meaningful for prolonged periods following iron dextran therapy because residual iron dextran may remain in the reticuloendothelial cells.

Bone scans involving 99m Tc-diphosphonate have been reported to show a dense, crescentic area of activity in the buttocks, following the contour of the iliac crest, 1 to 6 days after intramuscular injections of iron dextran.

Bone scans with 99m Tc-labeled bone seeking agents, in the presence of high serum ferritin levels or following iron dextran infusions, have been reported to show reduction of bony uptake, marked renal activity, and excessive blood pool and soft tissue accumulation.

Carcinogenesis, Mutagenesis, Impairment Of Fertility:

See WARNINGS.

Pregnancy:

Iron dextran has been shown to be teratogenic and embryocidal in mice, rats, rabbits, dogs, and monkeys when given in doses of about 3 times the maximum human dose.

No consistent adverse fetal effects were observed in mice, rats, rabbits, dogs and monkeys at doses of 50 mg iron/kg or less. Fetal and maternal toxicity has been reported in monkeys at a total intravenous dose of 90 mg iron/kg over a 14-day period. Similar effects were observed in mice and rats on administration of a single dose of 125 mg iron/kg. Fetal abnormalities in rats and dogs were observed at doses of 250 mg iron/kg and higher. The animals used in these tests were not iron deficient. There are no adequate and well-controlled studies in pregnant women. INFeD should be used during pregnancy only if the potential benefit justifies the potential risk to the fetus.

Placental Transfer:

Various animal studies and studies in pregnant humans have demonstrated inconclusive results with respect to the placental transfer of iron dextran as iron dextran. It appears that some iron does reach the fetus, but the form in which it crosses the placenta is not clear.

Nursing Mothers:

Caution should be exercised when INFeD is administered to a nursing woman. Traces of unmetabolized iron dextran are excreted in human milk.

Pediatric Use:

Not recommended for use in infants under 4 months of age. (See DOSAGE AND ADMINISTRATION.)

Close

ADVERSE REACTIONS

Severe/Fatal: Anaphylactic reactions have been reported with the use of iron dextran injection; on occasions these reactions have been fatal. Such reactions, which occur most often within the first several minutes of administration, have been generally characterized by sudden onset of respiratory difficulty and/or cardiovascular collapse. Because fatal anaphylactic reactions have been reported after administration of iron dextran injection, the drug should be given only when resuscitation techniques and treatment of anaphylactic and anaphylactoid shock are readily available. (See BOXED WARNING and PRECAUTIONS: General, pertaining to immediate availability of epinephrine.)

Cardiovascular: Chest pain, chest tightness, shock, cardiac arrest, hypotension, hypertension, tachycardia, bradycardia, flushing, arrhythmias. (Flushing and hypotension may occur from too rapid injections by the intravenous route.)

Dermatologic: Urticaria, pruritus, purpura, rash, cyanosis.

Gastrointestinal: Abdominal pain, nausea, vomiting, diarrhea.

Hematologic/lymphatic: Leucocytosis, lymphadenopathy.

Musculoskeletal/soft tissue: Arthralgia, arthritis (may represent reactivation in patients with quiescent rheumatoid arthritis - See PRECAUTIONS: General), myalgia; backache; sterile abscess, atrophy/fibrosis (intramuscular injection site); brown skin and/or underlying tissue discoloration (staining), soreness or pain at or near intramuscular injection sites; cellulitis; swelling; inflammation; local phlebitis at or near intravenous injection site.

Neurologic: Convulsions, seizures, syncope, headache, weakness, unresponsiveness, paresthesia, febrile episodes, chills, dizziness, disorientation, numbness, unconsciousness.

Respiratory: Respiratory arrest, dyspnea, bronchospasm, wheezing.

Urologic: Hematuria.

Delayed reactions: Arthralgia, backache, chills, dizziness, fever, headache, malaise, myalgia, nausea, vomiting. (See WARNINGS).

Miscellaneous: Febrile episodes, sweating, shivering, chills, malaise, altered taste.

OVERDOSAGE

Overdosage with iron dextran is unlikely to be associated with any acute manifestations. Dosages of iron dextran in excess of the requirements for restoration of hemoglobin and replenishment of iron stores may lead to hemosiderosis. Periodic monitoring of serum ferritin levels may be helpful in recognizing a deleterious progressive accumulation of iron resulting from impaired uptake of iron from the reticuloendothelial system in concurrent medical conditions such as chronic renal failure, Hodgkin’s disease, and rheumatoid arthritis. The LD50 of iron dextran is not less than 500 mg/kg in the mouse.

DOSAGE & ADMINISTRATION

Oral iron should be discontinued prior to administration of INFeD.

Dosage:

I. Iron Deficiency Anemia: Periodic hematologic determination (hemoglobin and hematocrit) is a simple and accurate technique for monitoring hematological response, and should be used as a guide in therapy. It should be recognized that iron storage may lag behind the appearance of normal blood morphology. Serum iron, total iron binding capacity (TIBC) and percent saturation of transferrin are other important tests for detecting and monitoring the iron deficient state.

After administration of iron dextran complex, evidence of a therapeutic response can be seen in a few days as an increase in the reticulocyte count.

Although serum ferritin is usually a good guide to body iron stores, the correlation of body iron stores and serum ferritin may not be valid in patients on chronic renal dialysis who are also receiving iron dextran complex.

Although there are significant variations in body build and weight distribution among males and females, the accompanying table and formula represent a convenient means for estimating the total iron required. This total iron requirement reflects the amount of iron needed to restore hemoglobin concentration to normal or near normal levels plus an additional allowance to provide adequate replenishment of iron stores in most individuals with moderately or severely reduced levels of hemoglobin. It should be remembered that iron deficiency anemia will not appear until essentially all iron stores have been depleted. Therapy, thus, should aim at not only replenishment of hemoglobin iron but iron stores as well.

Factors contributing to the formula are shown below.

a…Blood volume . . . . . . . . . . . . . . . .65 mL/kg of body weight

b. Normal hemoglobin (males and females)

over 15 kg (33 lbs) . . . . . . . . . . .14.8 g/dL

15 kg (33 lbs) or less . . . . . . . . .12.0 g/dL

c. Iron content of hemoglobin . . . . . 0.34%

d. Hemoglobin deficit

e. Weight

Based on the above factors, individuals with normal hemoglobin levels will have approximately 33 mg of blood iron per kilogram of body weight (15 mg/lb).

Note: The table and accompanying formula are applicable for dosage determinations only in patients with iron deficiency anemia; they are not to be used for dosage determinations in patients requiring iron replacement for blood loss.

TOTAL INFeD REQUIREMENT FOR HEMOGLOBIN RESTORATION AND IRON STORES REPLACEMENT*

*Table values were calculated based on a normal adult hemoglobin of 14.8 g/dL for weights greater than 15 kg (33 lbs) and a hemoglobin of 12.0 g/dL for weights less than or equal to 15 kg (33 lbs).

The total amount of INFeD in mL required to treat the anemia and replenish iron stores may be approximated as follows:

Adults and Children over 15 kg (33 lbs): See Dosage Table. Alternatively, the total dose may be calculated: Dose (mL) = 0.0442 (Desired Hb - Observed Hb) x LBW + (0.26 x LBW)

Based on: Desired Hb = the target Hb in g/dL.

Observed Hb = the patient’s current hemoglobin in g/dL.

LBW = Lean body weight in kg. A patient’s lean body weight (or actual body weight if less than lean body weight) should be utilized when determining dosage.

For males: LBW = 50 kg + 2.3 kg for each inch of patient’s height over 5 feet

For females: LBW = 45.5 kg + 2.3 kg for each inch of patient’s height over 5 feet

To calculate a patient's weight in kg when lbs are known:

INFeD should not normally be given in the first four months of life. (See PRECAUTIONS: Pediatric Use).

Alternatively, the total dose may be calculated:

Dose (mL) = 0.0442 (Desired Hb - Observed Hb) x W + (0.26 x W)

Based on: Desired Hb = the target Hb in g/dL.

(Normal Hb for Children 15 kg or less is 12 g/dL) W = Weight in kg.

To calculate a patient's weight in kg when lbs are known:

II. Iron Replacement for Blood Loss: Some individuals sustain blood losses on an intermittent or repetitive basis. Such blood losses may occur periodically in patients with hemorrhagic diatheses (familial telangiectasia; hemophilia; gastrointestinal bleeding) and on a repetitive basis from procedures such as renal hemodialysis.

Iron therapy in these patients should be directed toward replacement of the equivalent amount of iron represented in the blood loss. The table and formula described under I. Iron Deficiency Anemia are not applicable for simple iron replacement values.

Quantitative estimates of the individual’s periodic blood loss and hematocrit during the bleeding episode provide a convenient method for the calculation of the required iron dose.

The formula shown below is based on the approximation that 1 mL of normocytic, normochromic red cells contains 1 mg of elemental iron:

Replacement iron (in mg) = Blood loss (in mL) x hematocrit

Example: Blood loss of 500 mL with 20% hematocrit

Replacement Iron = 500 x 0.20 = 100 mg

Administration:

The total amount of INFeD required for the treatment of iron deficiency anemia or iron replacement for blood loss is determined from the table or appropriate formula. (See Dosage).

1. Intravenous Injection - PRIOR TO THE FIRST INTRAVENOUS INFeD THERAPEUTIC DOSE, ADMINISTER AN INTRAVENOUS TEST DOSE OF 0.5 ML. ADMINISTER THE TEST DOSE AT A GRADUAL RATE OVER AT LEAST 30 SECONDS. Although anaphylactic reactions known to occur following INFeD administration are usually evident within a few minutes, or sooner, it is recommended that a period of an hour or longer elapse before the remainder of the initial therapeutic dose is given.

Individual doses of 2 mL or less may be given on a daily basis until the calculated total amount required has been reached. INFeD is given undiluted at a slow gradual rate not to exceed 50 mg (1 mL) per minute.

2. Intramuscular Injection - PRIOR TO THE FIRST INTRAMUSCULAR INFeD THERAPEUTIC DOSE, ADMINISTER AN INTRAMUSCULAR TEST DOSE OF 0.5 ML. (See BOXED WARNING and PRECAUTIONS.) The test dose should be administered in the buttock using the same technique as described in the last paragraph of this section. Although anaphylactic reactions known to occur following INFeD administration are usually evident within a few minutes or sooner, it is recommended that at least an hour or longer elapse before the remainder of the initial therapeutic dose is given.

If no adverse reactions are observed, INFeD can be given according to the following schedule until the calculated total amount required has been reached. Each day’s dose should ordinarily not exceed 0.5 mL (25 mg of iron) for infants under 5 kg (11 lbs); 1.0 mL (50 mg of iron) for children under 10 kg (22 lbs); and 2.0 mL (100 mg of iron) for other patients.

INFeD should be injected only into the muscle mass of the upper outer quadrant of the buttock - never into the arm or other exposed areas - and should be injected deeply, with a 2-inch or 3-inch 19 or 20 gauge needle. If the patient is standing, he/she should be bearing his/her weight on the leg opposite the injection site, or if in bed, he/she should be in the lateral position with injection site uppermost. To avoid injection or leakage into the subcutaneous tissue, a Z-track technique (displacement of the skin laterally prior to injection) is recommended.

NOTE: Do not mix INFeD with other medications or add to parenteral nutrition solutions for intravenous infusion.

Parenteral drug products should be inspected visually for particulate matter and discoloration prior to administration, whenever the solution and container permit.

HOW SUPPLIED

INFED(R) (IRON DEXTRAN INJECTION, USP) is supplied in the following dosage forms.
NDC 51662-1441-1
INFED(R) (IRON DEXTRAN INJECTION, USP) 100mg elemental iron/2mL (50mg/mL) 2mL VIAL

HF Acquisition Co LLC, DBA HealthFirst
Mukilteo, WA 98275

Also supplied in the following manufacture supplied dosage forms

INFeD (Iron Dextran Injection USP) containing 50 mg of elemental iron per mL, is available in 2 mL single dose amber vials (for intramuscular or intravenous use) in cartons of 10 (NDC 0023-6082-10).

Store at 20 -25°C (68 -77°F) [See USP Controlled Room Temperature].

Rx Only

REFERENCES

Hatton RC, Portales IT, Finlay A, Ross EA. Removal of Iron Dextran by Hemodialysis: An In Vitro Study.
Am J Kid Dis. 1995; 26(2):327-330.
Manuel MA, Stewart WK, St. Clair Neill GD, Hutchinson F. Loss of Iron-Dextran through Cuprophane Membrane of a Disposable Coil Dialyser. Nephron. 1972;9:94-98.

For all medical inquiries contact:
Allergan
Medical Communications
1-800-678-1605

Distributed by:
Allergan USA, Inc.
Madison, NJ 07940

Manufactured by:
Patheon Italia S.p.A.
Ferentino, Italy 03013

© 2019 Allergan. All rights reserved.
INFED® is a registered trademark of Allergan Sales, LLC.
Allergan® and its design are trademarks of Allergan, Inc.

Content Updated: November 2018

v.1.1USPI6082